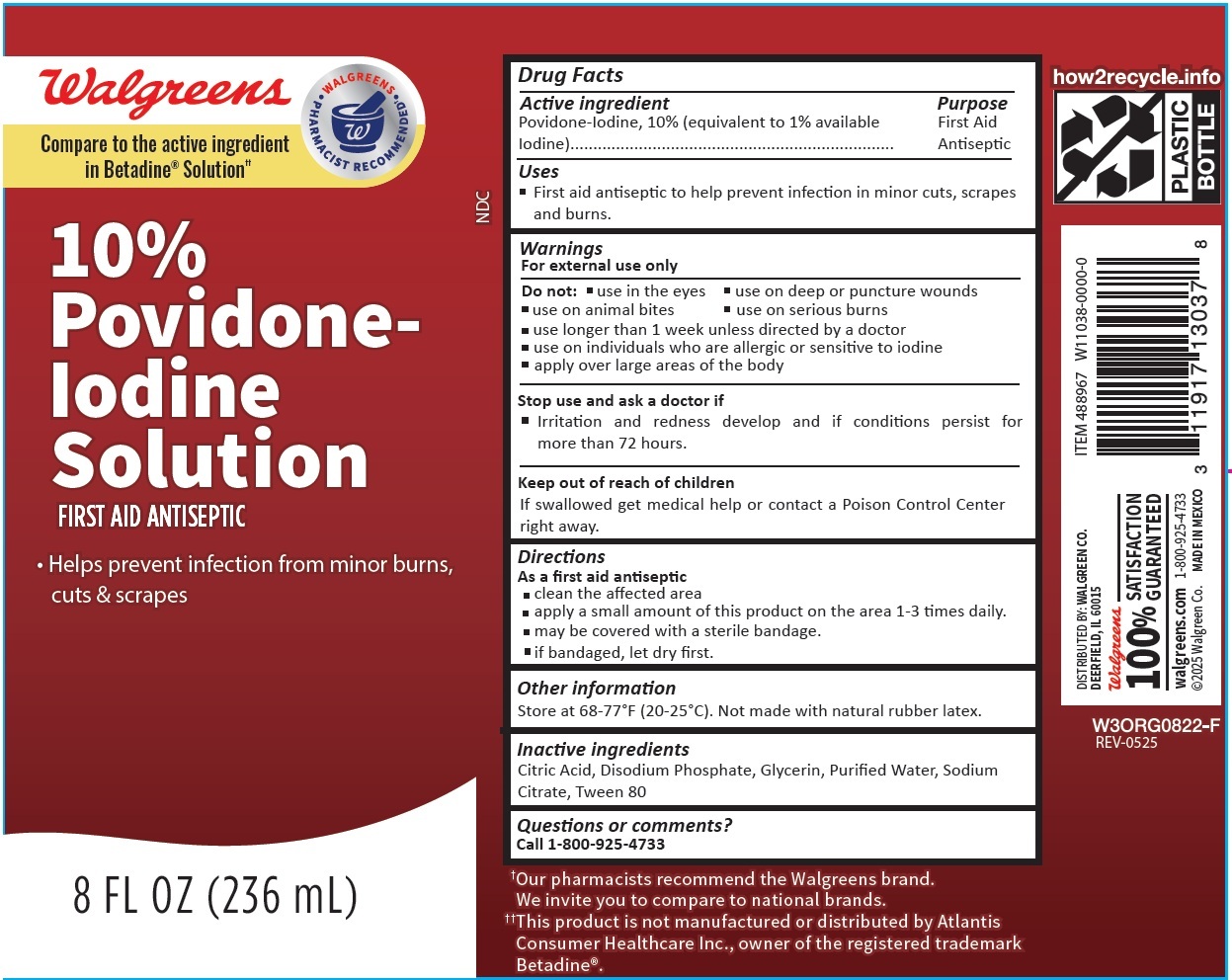 DRUG LABEL: Walgreens 10 Povidone-Iodine Solution
NDC: 0363-3736 | Form: LIQUID
Manufacturer: WALGREEN COMPANY
Category: otc | Type: HUMAN OTC DRUG LABEL
Date: 20250710

ACTIVE INGREDIENTS: POVIDONE-IODINE 100 mg/1 mL
INACTIVE INGREDIENTS: CITRIC ACID MONOHYDRATE; SODIUM PHOSPHATE, DIBASIC, ANHYDROUS; GLYCERIN; WATER; SODIUM CITRATE; POLYSORBATE 80

Walgreens 10% Povidone-Iodine Solution

Active Ingredient

Povidone-Iodine, 10% (equivalent to 1% available Iodine)

Purpose

First Aid Antiseptic

Uses

- First aid antiseptic to help prevent infection in minor cuts, scrapes and burns.

Warnings

For external use only

Do not:

• use in the eyes • use on deep or puncture wounds • use on animal bites • use on serious burns • use longer than 1 week unless directed by a doctor • use on individuals who are allergic or sensitive to iodine • apply over large areas of the body

Stop use and ask a doctor if

• Irritation and redness develop and if conditions persist for more than 72 hours.

Keep out of reach of children

If swallowed get medical help or contact a Poison Control Center right away.

Directions

As a first aid antiseptic

- clean the affected area
- apply a small amount of this product on the area 1-3 times daily.
- may be covered with a sterile bandage.
- if bandaged, let dry first.

Other information

Store at 68-77° F (20-25° C). Not made with natural rubber latex.

Inactive ingredients

Citric Acid, Disodium Phosphate, Glycerin, Purified Water, Sodium Citrate, Tween 80

Questions or Comments?

Call 1-800-925-4733